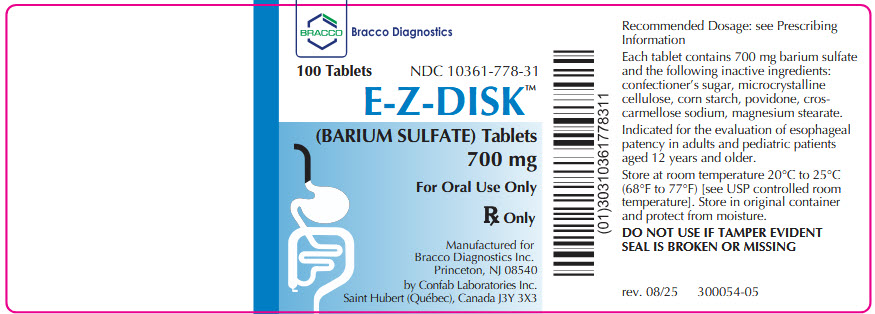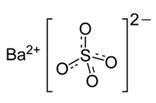 DRUG LABEL: E-Z-Disk
NDC: 10361-778 | Form: TABLET
Manufacturer: E-Z-EM, INC.
Category: prescription | Type: HUMAN PRESCRIPTION DRUG LABEL
Date: 20250929

ACTIVE INGREDIENTS: BARIUM SULFATE 700 mg/1 1

HIGHLIGHTS OF PRESCRIBING INFORMATION

These highlights do not include all the information needed to use
E-Z-DISK safely and effectively. See full prescribing information for
E-Z-DISK.
E-Z-DISK (barium sulfate) tablets, for oral use
Initial U.S. Approval: 2016

1 INDICATIONS AND USAGE

E-Z-DISK is a radiographic contrast agent indicated for the evaluation of esophageal patency in adults and pediatric patients aged 12 years and older. (1)

2 DOSAGE AND ADMINISTRATION

- The recommended dose is one 700 mg tablet orally during imaging.
- Swallow one tablet whole with the aid of one or two swallows of water. Do not cut, crush, or chew the tablet. (2)

3 DOSAGE FORMS AND STRENGTHS

Tablets: 700 mg of barium sulfate (3)

4 CONTRAINDICATIONS

- Known severe hypersensitivity to barium sulfate or any of the excipients of E-Z-DISK (4)
- Known or suspected perforation of the gastrointestinal (GI) tract or conditions associated with high risk of GI perforation (4)
- Known obstruction of the GI tract (4)
- Conditions associated with high risk of aspiration (4)

5 WARNINGS AND PRECAUTIONS

- Hypersensitivity Reactions: Have emergency equipment and trained personnel immediately available during the procedure. (5.1)
- Intra-abdominal Barium Leakage: Barium leakage may occur in conditions such as GI fistula, ulcer, inflammatory bowel disease, appendicitis, diverticulitis, and severe stenosis or obstructing lesions of the GI tract and has been associated with peritonitis and granuloma formation. (5.2)
- Baroliths and Bowel Obstruction: Maintain adequate hydration following a barium sulfate procedure and monitor patients at risk for delayed GI transit for development of signs and symptoms of bowel obstruction. (5.3)
- Aspiration Pneumonitis: Patients with a history of food aspiration or compromised swallowing mechanism may be at high risk. (5.4)

6 ADVERSE REACTIONS

Common adverse reactions include nausea, vomiting, diarrhea, and abdominal cramping. (6)

To report SUSPECTED ADVERSE REACTIONS, contact Bracco Diagnostics Inc at 1-800-257-5181 or FDA at 1-800-FDA-1088 or www.fda.gov/medwatch

FULL PRESCRIBING INFORMATION

1 INDICATIONS AND USAGE

E-Z-DISK is indicated for the evaluation of esophageal patency in adults and pediatric patients aged 12 years and older.

2 DOSAGE AND ADMINISTRATION

The recommended dose of E-Z-DISK in adults and pediatric patients aged 12 years and older is one 700 mg tablet orally during imaging.

Swallow one tablet whole with the aid of one or two swallows of water. Do not cut, crush, or chew the tablet.

Advise patients to hydrate following the E-Z-DISK imaging procedure [see Warnings and Precautions (5.3)].

E-Z-DISK is formulated to disintegrate within the gastrointestinal (GI) tract. In the event of prolonged retention, consider implementing appropriate interventions.

3 DOSAGE FORMS AND STRENGTHS

Tablets: 700 mg of barium sulfate as a white to lightly colored, between 11.5 mm and 13.5 mm (0.45 inch and 0.53 inch) in diameter, flat-sided disk with EZEM inscribed on one side and 778 on the other side.

4 CONTRAINDICATIONS

E-Z-DISK is contraindicated in patients with:

- Known severe hypersensitivity to barium sulfate or any of the excipients of E-Z-DISK [see Warnings and Precautions (5.1)]
- Known, suspected, or high risk of perforation of the GI tract such as patients with a recent GI perforation, acute GI hemorrhage or ischemia, toxic megacolon, severe ileus, recent GI surgery or biopsy, acute GI injury, or recent radiotherapy to the pelvis [see Warnings and Precautions (5.2)]
- Known obstruction of the GI tract [see Warnings and Precautions (5.3)]
- High risk of aspiration such as patients with known or suspected tracheoesophageal fistula or obtundation [see Warnings and Precautions (5.4)]

5 WARNINGS AND PRECAUTIONS

5.1 Hypersensitivity Reactions

E-Z-DISK may induce serious hypersensitivity reactions with manifestations including hypotension, bronchospasm and other respiratory impairments, and dermal reactions including rashes, urticaria and itching. A history of bronchial asthma, atopy, food allergies, or a reaction to a contrast agent may increase the risk for hypersensitivity reactions. E-Z-DISK is contraindicated in patients with known severe hypersensitivity to barium sulfate or any of the excipients of E-Z-DISK [see Contraindications (4)]. Have emergency equipment and trained personnel immediately available during the procedure.

5.2 Intra-abdominal Barium Leakage

Barium leakage from the GI tract has been associated with peritonitis and granuloma formation. Barium sulfate from orally administered E-Z-DISK may leak in the presence of conditions such as carcinomas, GI fistula, inflammatory bowel disease, gastric or duodenal ulcer, appendicitis, or diverticulitis, and in patients with severe stenosis of the GI tract, especially if it is distal to the stomach. E-Z-DISK is contraindicated in patients with known, suspected, or high risk of perforation of the GI tract [see Contraindications (4)].

5.3 Baroliths and Bowel Obstruction

Barium sulfate from orally administered E-Z-DISK may accumulate in the GI tract, causing obstruction or impaction with development of baroliths (inspissated barium associated with feces) and may lead to abdominal pain, appendicitis, or perforation. Patients with the following are at higher risk for developing obstruction or baroliths: severe stenosis at any level of the GI tract, impaired GI motility, electrolyte imbalance, dehydration, low residue diet, medications that delay GI motility, constipation, pediatric patients with cystic fibrosis or Hirschsprung disease, and advanced age. E-Z-DISK is contraindicated in patients with known obstruction of the GI tract [see Contraindications (4)]. To reduce the risk of delayed GI transit and obstruction, maintain adequate hydration after the E-Z-DISK procedure. Monitor patients at risk for delayed gastrointestinal transit for development of signs and symptoms of bowel obstruction.

5.4 Aspiration Pneumonitis

Oral administration of barium is associated with aspiration pneumonitis, especially in patients with a history of food aspiration or with compromised swallowing mechanism. Vomiting following oral administration of barium sulfate may lead to aspiration pneumonitis. E-Z-DISK is contraindicated in patients with high risk of aspiration such as known or suspected tracheoesophageal fistula or obtundation [see Contraindications (4)].

5.5 Systemic Embolization

Barium sulfate from orally administered E-Z-DISK may intravasate into the venous drainage of the GI tract and enter the circulation as a "barium embolus" leading to potentially fatal complications, which include systemic and pulmonary embolism, disseminated intravascular coagulation, septicemia, and prolonged severe hypotension.

6 ADVERSE REACTIONS

The following clinically significant adverse reactions are described elsewhere in the labeling:

- Hypersensitivity Reactions [see Warnings and Precautions (5.1)]
- Intra-abdominal Barium Leakage [see Warnings and Precautions (5.2)]
- Baroliths and Bowel Obstruction [see Warnings and Precautions (5.3)]
- Aspiration Pneumonitis [see Warnings and Precautions (5.4)]

The following adverse reactions associated with the use of E-Z-DISK or other barium sulfate products were identified in postmarketing reports or published clinical studies. Because some of these reactions are reported voluntarily from a population of uncertain size, it is not always possible to reliably estimate their frequency or to establish a causal relationship to drug exposure:

Cardiovascular disorders: Vasovagal and syncopal episodes
Gastrointestinal disorders: Barium sulfate impaction, nausea, vomiting, diarrhea, abdominal cramping
Respiratory disorders: Aspiration pneumonitis

Adverse Reactions in Pediatric Patients

No additional safety signals have been reported in pediatric patients aged 12 years and older.

8 USE IN SPECIFIC POPULATIONS

8.1 Pregnancy

Risk Summary

Barium sulfate is not absorbed systemically following oral administration, and maternal use is not expected to result in fetal exposure to E-Z-DISK [see Clinical Pharmacology (12.3)]

8.2 Lactation

Risk Summary

Barium sulfate is not absorbed systemically by the mother following oral administration, and breastfeeding is not expected to result in exposure of the infant to E-Z-DISK.

8.4 Pediatric Use

The safety and effectiveness of E-Z-DISK for use in radiographic evaluation of esophageal patency have been established in pediatric patients 12 years and older. Use of E-Z-DISK in this age group for this indication is supported by effectiveness established in studies of adults and pediatric safety data from other barium sulfate products [see Adverse Reactions (6)].

8.5 Geriatric use

Reported clinical experience has not identified differences between elderly and younger patients.

11 DESCRIPTION

E-Z-DISK (barium sulfate) tablet is a radiographic contrast agent for oral use.

Barium sulfate is designated chemically as BaSO4 with molecular weight of 233.4 g/mol, density of 4.5 g/cm^3, and the following chemical structure:

E-Z-DISK is a white to lightly colored, flat-sided disk, between 11.5 mm and 13.5 mm (0.45 inch and 0.53 inch) in diameter. Each tablet contains 700 mg barium sulfate and the following inactive ingredients: confectioner’s sugar, microcrystalline cellulose, corn starch, povidone, croscarmellose sodium, and magnesium stearate.

12 CLINICAL PHARMACOLOGY

12.1 Mechanism of Action

E-Z-DISK is formulated to pass through the esophagus into the stomach when the esophageal lumen is greater than 11.5 mm to 13.5 mm (0.45 inch to 0.53 inch) in diameter. Due to its high atomic number, barium is opaque to X-rays and therefore acts as a positive contrast agent for radiographic studies.

12.2 Pharmacodynamics

Barium sulfate has no pharmacological effects.

12.3 Pharmacokinetics

Orally administered barium sulfate passes through the gastrointestinal tract in an unchanged form and is absorbed only in insignificant amounts.

13 NONCLINICAL TOXICOLOGY

13.1 Carcinogenesis, Mutagenesis, Impairment of Fertility

No animal studies have been performed to evaluate the carcinogenic potential of barium sulfate or potential effects on fertility.

16 HOW SUPPLIED/STORAGE AND HANDLING

How Supplied

E-Z-DISK (barium sulfate) tablets, 700 mg, are white to lightly colored, between 11.5 mm and 13.5 mm (0.45 inch and 0.53 inch) in diameter, flat-sided disks with EZEM inscribed on one side and 778 on the other side supplied in a glass bottle containing 100 tablets (NDC 10361-778-31).

Storage and Handling

Store at 20°C to 25°C (68°F to 77° F) [see USP controlled room temperature]. Store in original container and protect from moisture.

17 PATIENT COUNSELING INFORMATION

Administration Instructions

Instruct patients to swallow E-Z-DISK as a whole tablet with the aid of one or two swallows of water (do not cut, crush, or chew) [see Dosage and Administration (2.2)].

Hypersensitivity Reactions

Advise patients to seek medical attention for any delayed onset of hypersensitivity such as rash, urticaria, or respiratory difficulty [see Warnings and Precautions (5.1)].

Baroliths and Bowel Obstruction

Advise patients to drink a sufficient amount of water to maintain adequate hydration following the E-Z-DISK procedure and to seek medical attention for signs and symptoms of bowel obstruction [see Warnings and Precautions (5.3)].

Manufactured for
Bracco Diagnostics Inc.
Princeton, NJ 08540

by
Confab Laboratories Inc.
Saint Hubert (Quebec) Canada J3Y 3X3

rev. 08/25 301871-02

PACKAGE LABEL

E-Z-Disk Tablets NDC: 10361-778-3